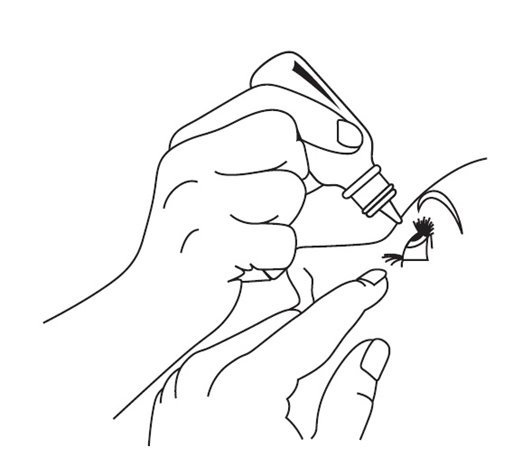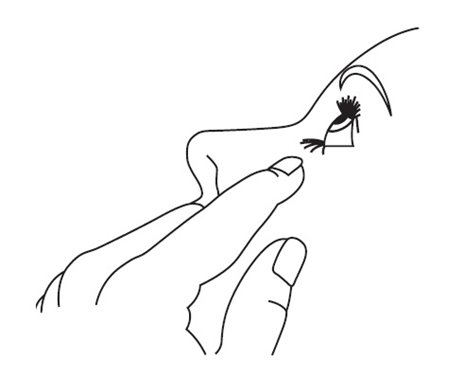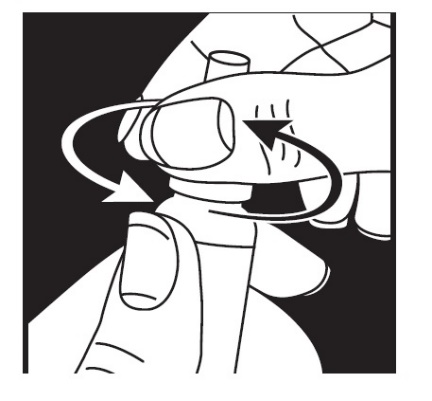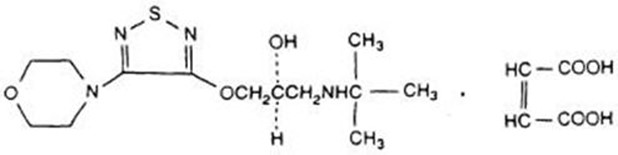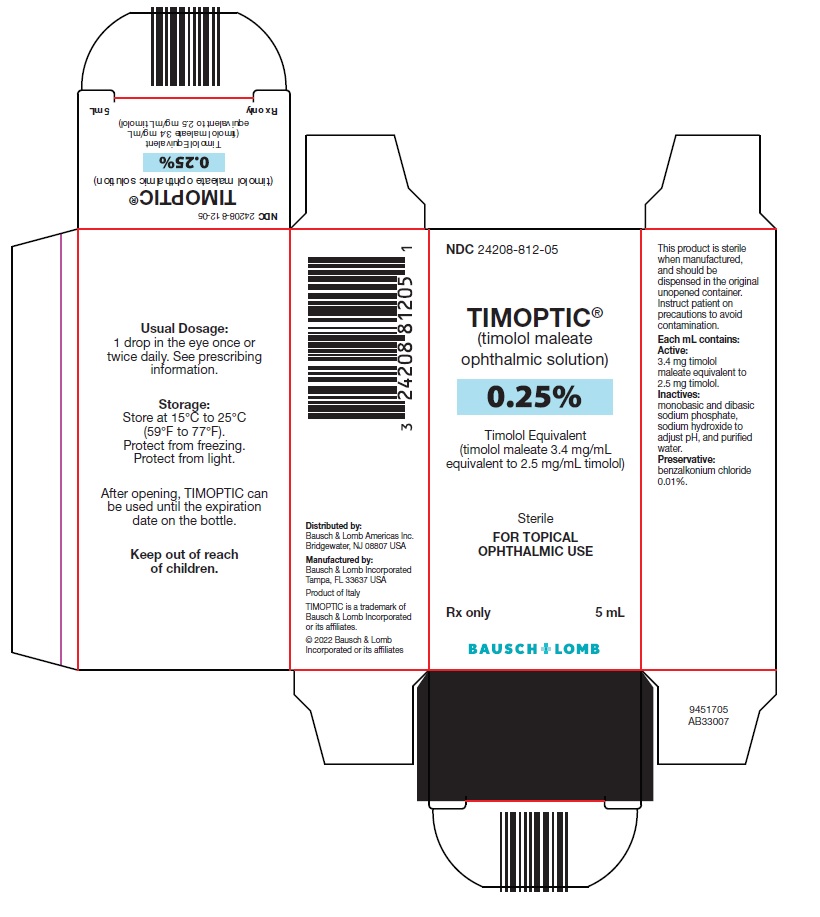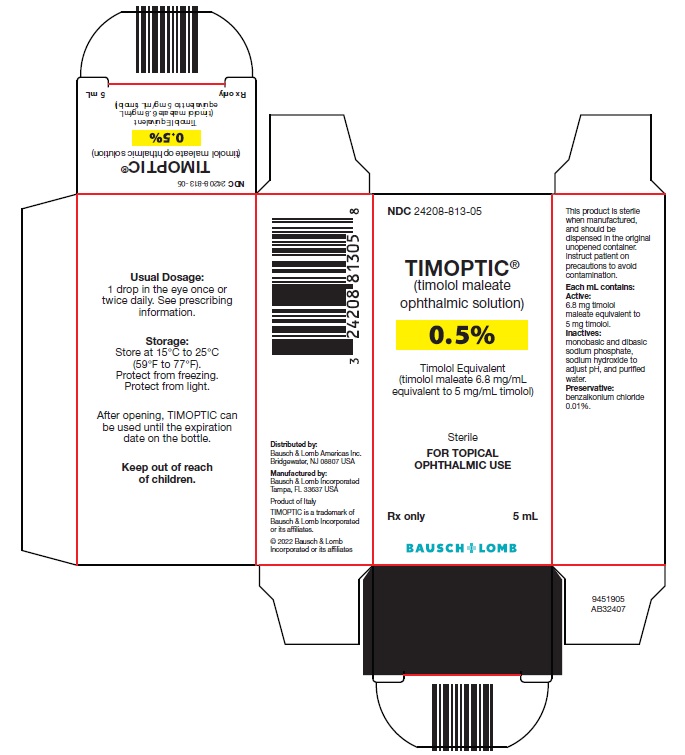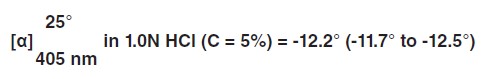 DRUG LABEL: Timoptic
NDC: 24208-812 | Form: SOLUTION
Manufacturer: Bausch & Lomb Incorporated
Category: prescription | Type: HUMAN PRESCRIPTION DRUG LABEL
Date: 20220430

ACTIVE INGREDIENTS: Timolol Maleate 2.5 mg/1 mL
INACTIVE INGREDIENTS: SODIUM PHOSPHATE, MONOBASIC, UNSPECIFIED FORM; SODIUM PHOSPHATE, DIBASIC, UNSPECIFIED FORM; Sodium Hydroxide; Water; Benzalkonium Chloride

TIMOPTIC® 0.25% and 0.5%
(timolol maleate ophthalmic solution)

DESCRIPTION

TIMOPTIC® (timolol maleate ophthalmic solution) is a non-selective beta-adrenergic receptor blocking agent. Its chemical name is (-)-1-(tert-butylamino)-3-[(4-morpholino-1,2,5-thiadiazol-3-yl)oxy]-2-propanol maleate (1:1) (salt). Timolol maleate possesses an asymmetric carbon atom in its structure and is provided as the levo-isomer. The optical rotation of timolol maleate is:

Its molecular formula is C13H24N4O3S•C4H4O4 and its structural formula is:

Timolol maleate has a molecular weight of 432.50. It is a white, odorless, crystalline powder which is soluble in water; sparingly soluble in ethanol; slightly soluble in chloroform; practically insoluble in ether. TIMOPTIC is stable at room temperature.

TIMOPTIC Ophthalmic Solution is supplied as a sterile, isotonic, buffered, aqueous solution of timolol maleate in two dosage strengths. Each mL of TIMOPTIC 0.25% contains 2.5 mg of timolol (3.4 mg of timolol maleate). The pH of the solution is approximately 7, and the osmolality is 260-340 mOsm/kg. Each mL of TIMOPTIC 0.5% contains 5 mg of timolol (6.8 mg of timolol maleate). Inactive ingredients: monobasic and dibasic sodium phosphate, sodium hydroxide to adjust pH, and purified water. Benzalkonium chloride 0.01% is added as preservative.

CLINICAL PHARMACOLOGY

Mechanism of Action

Timolol maleate is a beta1 and beta2 (non-selective) adrenergic receptor blocking agent that does not have significant intrinsic sympathomimetic, direct myocardial depressant, or local anesthetic (membrane-stabilizing) activity.

Beta-adrenergic receptor blockade reduces cardiac output in both healthy subjects and patients with heart disease. In patients with severe impairment of myocardial function, beta-adrenergic receptor blockade may inhibit the stimulatory effect of the sympathetic nervous system necessary to maintain adequate cardiac function.

Beta-adrenergic receptor blockade in the bronchi and bronchioles results in increased airway resistance from unopposed parasympathetic activity. Such an effect in patients with asthma or other bronchospastic conditions is potentially dangerous.

TIMOPTIC Ophthalmic Solution, when applied topically on the eye, has the action of reducing elevated as well as normal intraocular pressure, whether or not accompanied by glaucoma. Elevated intraocular pressure is a major risk factor in the pathogenesis of glaucomatous visual field loss. The higher the level of intraocular pressure, the greater the likelihood of glaucomatous visual field loss and optic nerve damage.

The onset of reduction in intraocular pressure following administration of TIMOPTIC can usually be detected within one-half hour after a single dose. The maximum effect usually occurs in one to two hours and significant lowering of intraocular pressure can be maintained for periods as long as 24 hours with a single dose. Repeated observations over a period of one year indicate that the intraocular pressure-lowering effect of TIMOPTIC is well maintained.

The precise mechanism of the ocular hypotensive action of TIMOPTIC is not clearly established at this time. Tonography and fluorophotometry studies in man suggest that its predominant action may be related to reduced aqueous formation. However, in some studies a slight increase in outflow facility was also observed.

Pharmacokinetics

In a study of plasma drug concentration in six subjects, the systemic exposure to timolol was determined following twice daily administration of TIMOPTIC 0.5%. The mean peak plasma concentration following morning dosing was 0.46 ng/mL and following afternoon dosing was 0.35 ng/mL.

Clinical Studies

In controlled multiclinic studies in patients with untreated intraocular pressures of 22 mmHg or greater, TIMOPTIC 0.25% or 0.5% administered twice a day produced a greater reduction in intraocular pressure than 1, 2, 3, or 4% pilocarpine solution administered four times a day or 0.5, 1, or 2% epinephrine hydrochloride solution administered twice a day.

In these studies, TIMOPTIC was generally well tolerated and produced fewer and less severe side effects than either pilocarpine or epinephrine. A slight reduction of resting heart rate in some patients receiving TIMOPTIC (mean reduction 2.9 beats/minute standard deviation 10.2) was observed.

INDICATIONS AND USAGE

TIMOPTIC Ophthalmic Solution is indicated in the treatment of elevated intraocular pressure in patients with ocular hypertension or open-angle glaucoma.

CONTRAINDICATIONS

TIMOPTIC is contraindicated in patients with (1) bronchial asthma; (2) a history of bronchial asthma; (3) severe chronic obstructive pulmonary disease [see WARNINGS]; (4) sinus bradycardia; (5) second or third degree atrioventricular block; (6) overt cardiac failure [see WARNINGS]; (7) cardiogenic shock; or (8) hypersensitivity to any component of this product.

WARNINGS

As with many topically applied ophthalmic drugs, this drug is absorbed systemically.

The same adverse reactions found with systemic administration of beta-adrenergic blocking agents may occur with topical administration. For example, severe respiratory reactions and cardiac reactions, including death due to bronchospasm in patients with asthma, and rarely death in association with cardiac failure, have been reported following systemic or ophthalmic administration of timolol maleate [see CONTRAINDICATIONS].

Cardiac Failure

Sympathetic stimulation may be essential for support of the circulation in individuals with diminished myocardial contractility, and its inhibition of beta-adrenergic receptor blockade may precipitate more severe failure.

In Patients Without a History of Cardiac Failure continued depression of the myocardium with beta-blocking agents over a period of time can, in some cases, lead to cardiac failure. At the first sign or symptom of cardiac failure, TIMOPTIC should be discontinued.

Obstructive Pulmonary Disease

Patients with chronic obstructive pulmonary disease (e.g., chronic bronchitis, emphysema) of mild or moderate severity, bronchospastic disease, or a history of bronchospastic disease (other than bronchial asthma or a history of bronchial asthma, in which TIMOPTIC is contraindicated [see CONTRAINDICATIONS]) should, in general, not receive beta-blockers, including TIMOPTIC.

Major Surgery

The necessity or desirability of withdrawal of beta-adrenergic blocking agents prior to major surgery is controversial. Beta-adrenergic receptor blockade impairs the ability of the heart to respond to beta-adrenergically mediated reflex stimuli. This may augment the risk of general anesthesia in surgical procedures. Some patients receiving beta-adrenergic receptor blocking agents have experienced protracted severe hypotension during anesthesia. Difficulty in restarting and maintaining the heartbeat has also been reported. For these reasons, in patients undergoing elective surgery, some authorities recommend gradual withdrawal of beta-adrenergic receptor blocking agents.

If necessary during surgery, the effects of beta-adrenergic blocking agents may be reversed by sufficient doses of adrenergic agonists.

Diabetes Mellitus

Beta-adrenergic blocking agents should be administered with caution in patients subject to spontaneous hypoglycemia or to diabetic patients (especially those with labile diabetes) who are receiving insulin or oral hypoglycemic agents. Beta-adrenergic receptor blocking agents may mask the signs and symptoms of acute hypoglycemia.

Thyrotoxicosis

Beta-adrenergic blocking agents may mask certain clinical signs (e.g., tachycardia) of hyperthyroidism. Patients suspected of developing thyrotoxicosis should be managed carefully to avoid abrupt withdrawal of beta-adrenergic blocking agents that might precipitate a thyroid storm.

PRECAUTIONS

General

Because of potential effects of beta-adrenergic blocking agents on blood pressure and pulse, these agents should be used with caution in patients with cerebrovascular insufficiency. If signs or symptoms suggesting reduced cerebral blood flow develop following initiation of therapy with TIMOPTIC, alternative therapy should be considered.

There have been reports of bacterial keratitis associated with the use of multiple-dose containers of topical ophthalmic products. These containers had been inadvertently contaminated by patients who, in most cases, had a concurrent corneal disease or a disruption of the ocular epithelial surface [see PRECAUTIONS, Information for Patients].

Choroidal detachment after filtration procedures has been reported with the administration of aqueous suppressant therapy (e.g., timolol).

Angle-closure glaucoma:

In patients with angle-closure glaucoma, the immediate objective of treatment is to reopen the angle. This requires constricting the pupil. Timolol maleate has little or no effect on the pupil. TIMOPTIC should not be used alone in the treatment of angle-closure glaucoma.

Anaphylaxis:

While taking beta-blockers, patients with a history of atopy or a history of severe anaphylactic reactions to a variety of allergens may be more reactive to repeated accidental, diagnostic, or therapeutic challenge with such allergens. Such patients may be unresponsive to the usual doses of epinephrine used to treat anaphylactic reactions.

Muscle Weakness:

Beta-adrenergic blockade has been reported to potentiate muscle weakness consistent with certain myasthenic symptoms (e.g., diplopia, ptosis, and generalized weakness). Timolol has been reported rarely to increase muscle weakness in some patients with myasthenia gravis or myasthenic symptoms.

Information for Patients

Patients should be instructed to avoid allowing the tip of the dispensing container to contact the eye or surrounding structures.

Patients should also be instructed that ocular solutions, if handled improperly or if the tip of the dispensing container contacts the eye or surrounding structures, can become contaminated by common bacteria known to cause ocular infections. Serious damage to the eye and subsequent loss of vision may result from using contaminated solutions [see PRECAUTIONS, General].

Patients should also be advised that if they have ocular surgery or develop an intercurrent ocular condition (e.g., trauma or infection), they should immediately seek their physician's advice concerning the continued use of the present multidose container.

Patients with bronchial asthma, a history of bronchial asthma, severe chronic obstructive pulmonary disease, sinus bradycardia, second or third degree atrioventricular block, or cardiac failure should be advised not to take this product [see CONTRAINDICATIONS].

Patients should be advised that TIMOPTIC contains benzalkonium chloride which may be absorbed by soft contact lenses. Contact lenses should be removed prior to administration of the solution. Lenses may be reinserted 15 minutes following TIMOPTIC administration.

Drug Interactions

Although TIMOPTIC used alone has little or no effect on pupil size, mydriasis resulting from concomitant therapy with TIMOPTIC and epinephrine has been reported occasionally.

Beta-adrenergic blocking agents:

Patients who are receiving a beta-adrenergic blocking agent orally and TIMOPTIC should be observed for potential additive effects of beta-blockade, both systemic and on intraocular pressure. The concomitant use of two topical beta-adrenergic blocking agents is not recommended.

Calcium antagonists:

Caution should be used in the coadministration of beta-adrenergic blocking agents, such as TIMOPTIC, and oral or intravenous calcium antagonists because of possible atrioventricular conduction disturbances, left ventricular failure, and hypotension. In patients with impaired cardiac function, coadministration should be avoided.

Catecholamine-depleting drugs:

Close observation of the patient is recommended when a beta-blocker is administered to patients receiving catecholamine-depleting drugs such as reserpine, because of possible additive effects and the production of hypotension and/or marked bradycardia, which may result in vertigo, syncope, or postural hypotension.

Digitalis and calcium antagonists:

The concomitant use of beta-adrenergic blocking agents with digitalis and calcium antagonists may have additive effects in prolonging atrioventricular conduction time.

CYP2D6 inhibitors:

Potentiated systemic beta-blockade (e.g., decreased heart rate, depression) has been reported during combined treatment with CYP2D6 inhibitors (e.g., quinidine, SSRIs) and timolol.

Clonidine:

Oral beta-adrenergic blocking agents may exacerbate the rebound hypertension which can follow the withdrawal of clonidine. There have been no reports of exacerbation of rebound hypertension with ophthalmic timolol maleate.

Injectable epinephrine:

[see PRECAUTIONS, General, Anaphylaxis].

Carcinogenesis, Mutagenesis, Impairment of Fertility

In a two-year study of timolol maleate administered orally to rats, there was a statistically significant increase in the incidence of adrenal pheochromocytomas in male rats administered 300 mg/kg/day (approximately 42,000 times the systemic exposure following the maximum recommended human ophthalmic dose). Similar differences were not observed in rats administered oral doses equivalent to approximately 14,000 times the maximum recommended human ophthalmic dose.

In a lifetime oral study in mice, there were statistically significant increases in the incidence of benign and malignant pulmonary tumors, benign uterine polyps and mammary adenocarcinomas in female mice at 500 mg/kg/day, (approximately 71,000 times the systemic exposure following the maximum recommended human ophthalmic dose), but not at 5 or 50 mg/kg/day (approximately 700 or 7,000, respectively, times the systemic exposure following the maximum recommended human ophthalmic dose). In a subsequent study in female mice, in which post-mortem examinations were limited to the uterus and the lungs, a statistically significant increase in the incidence of pulmonary tumors was again observed at 500 mg/kg/day.

The increased occurrence of mammary adenocarcinomas was associated with elevations in serum prolactin which occurred in female mice administered oral timolol at 500 mg/kg/day, but not at doses of 5 or 50 mg/kg/day. An increased incidence of mammary adenocarcinomas in rodents has been associated with administration of several other therapeutic agents that elevate serum prolactin, but no correlation between serum prolactin levels and mammary tumors has been established in humans. Furthermore, in adult human female subjects who received oral dosages of up to 60 mg of timolol maleate (the maximum recommended human oral dosage), there were no clinically meaningful changes in serum prolactin.

Timolol maleate was devoid of mutagenic potential when tested in vivo (mouse) in the micronucleus test and cytogenetic assay (doses up to 800 mg/kg) and in vitro in a neoplastic cell transformation assay (up to 100 mcg/mL). In Ames tests the highest concentrations of timolol employed, 5,000 or 10,000 mcg/plate, were associated with statistically significant elevations of revertants observed with tester strain TA100 (in seven replicate assays), but not in the remaining three strains. In the assays with tester strain TA100, no consistent dose response relationship was observed, and the ratio of test to control revertants did not reach 2. A ratio of 2 is usually considered the criterion for a positive Ames test.

Reproduction and fertility studies in rats demonstrated no adverse effect on male or female fertility at doses up to 21,000 times the systemic exposure following the maximum recommended human ophthalmic dose.

Pregnancy

Teratogenic Effects - Teratogenicity studies with timolol in mice, rats, and rabbits at oral doses up to 50 mg/kg/day (7,000 times the systemic exposure following the maximum recommended human ophthalmic dose) demonstrated no evidence of fetal malformations. Although delayed fetal ossification was observed at this dose in rats, there were no adverse effects on postnatal development of offspring. Doses of 1,000 mg/kg/day (142,000 times the systemic exposure following the maximum recommended human ophthalmic dose) were maternotoxic in mice and resulted in an increased number of fetal resorptions. Increased fetal resorptions were also seen in rabbits at doses of 14,000 times the systemic exposure following the maximum recommended human ophthalmic dose, in this case without apparent maternotoxicity.

There are no adequate and well-controlled studies in pregnant women. TIMOPTIC should be used during pregnancy only if the potential benefit justifies the potential risk to the fetus.

Nursing Mothers

Timolol maleate has been detected in human milk following oral and ophthalmic drug administration. Because of the potential for serious adverse reactions from TIMOPTIC in nursing infants, a decision should be made whether to discontinue nursing or to discontinue the drug, taking into account the importance of the drug to the mother.

Pediatric Use

Safety and effectiveness of timolol maleate ophthalmic solution have been established when administered in pediatric patients aged 2 years and older. Use of timolol maleate ophthalmic solution in these children is supported by evidence from adequate and well controlled studies in children and adults. Safety and efficacy in pediatric patients below the age of 2 years have not been established.

Geriatric Use

No overall differences in safety or effectiveness have been observed between elderly and younger patients.

ADVERSE REACTIONS

The most frequently reported adverse experiences have been burning and stinging upon instillation (approximately one in eight patients).

The following additional adverse experiences have been reported less frequently with ocular administration of this or other timolol maleate formulations:

Body as a Whole

Headache, asthenia/fatigue, and chest pain.

Cardiovascular

Bradycardia, arrhythmia, hypotension, hypertension, syncope, heart block, cerebral vascular accident, cerebral ischemia, cardiac failure, worsening of angina pectoris, palpitation, cardiac arrest, pulmonary edema, edema, claudication, Raynaud's phenomenon, and cold hands and feet.

Digestive

Nausea, diarrhea, dyspepsia, anorexia, and dry mouth.

Immunologic

Systemic lupus erythematosus.

Nervous System/Psychiatric

Dizziness, increase in signs and symptoms of myasthenia gravis, paresthesia, somnolence, insomnia, nightmares, behavioral changes and psychic disturbances including depression, confusion, hallucinations, anxiety, disorientation, nervousness, and memory loss.

Skin

Alopecia and psoriasiform rash or exacerbation of psoriasis.

Hypersensitivity

Signs and symptoms of systemic allergic reactions, including anaphylaxis, angioedema, urticaria, and localized and generalized rash.

Respiratory

Bronchospasm (predominantly in patients with preexisting bronchospastic disease), respiratory failure, dyspnea, nasal congestion, cough and upper respiratory infections.

Endocrine

Masked symptoms of hypoglycemia in diabetic patients [see WARNINGS].

Special Senses

Signs and symptoms of ocular irritation including conjunctivitis, blepharitis, keratitis, ocular pain, discharge (e.g., crusting), foreign body sensation, itching and tearing, and dry eyes; ptosis; decreased corneal sensitivity; cystoid macular edema; visual disturbances including refractive changes and diplopia; pseudopemphigoid; choroidal detachment following filtration surgery [see PRECAUTIONS, General]; and tinnitus.

Urogenital

Retroperitoneal fibrosis, decreased libido, impotence, and Peyronie's disease.

The following additional adverse effects have been reported in clinical experience with ORAL timolol maleate or other ORAL beta-blocking agents and may be considered potential effects of ophthalmic timolol maleate: Allergic: Erythematous rash, fever combined with aching and sore throat, laryngospasm with respiratory distress; Body as a Whole: Extremity pain, decreased exercise tolerance, weight loss; Cardiovascular: Worsening of arterial insufficiency, vasodilatation; Digestive: Gastrointestinal pain, hepatomegaly, vomiting, mesenteric arterial thrombosis, ischemic colitis; Hematologic: Nonthrombocytopenic purpura; thrombocytopenic purpura, agranulocytosis; Endocrine: Hyperglycemia, hypoglycemia; Skin: Pruritus, skin irritation, increased pigmentation, sweating; Musculoskeletal: Arthralgia; Nervous System/Psychiatric: Vertigo, local weakness, diminished concentration, reversible mental depression progressing to catatonia, an acute reversible syndrome characterized by disorientation for time and place, emotional lability, slightly clouded sensorium, and decreased performance on neuropsychometrics; Respiratory: Rales, bronchial obstruction; Urogenital: Urination difficulties.

To report SUSPECTED ADVERSE REACTIONS, contact Bausch & Lomb Incorporated at 1-800-553-5340 or FDA at 1-800-FDA-1088 or www.fda.gov/medwatch.

OVERDOSAGE

There have been reports of inadvertent overdosage with TIMOPTIC Ophthalmic Solution resulting in systemic effects similar to those seen with systemic beta-adrenergic blocking agents such as dizziness, headache, shortness of breath, bradycardia, bronchospasm, and cardiac arrest [see ADVERSE REACTIONS].

Overdosage has been reported with timolol maleate tablets. A 30-year-old female ingested 650 mg of timolol maleate tablets (maximum recommended oral daily dose is 60 mg) and experienced second and third degree heart block. She recovered without treatment but approximately two months later developed irregular heartbeat, hypertension, dizziness, tinnitus, faintness, increased pulse rate, and borderline first degree heart block.

An in vitro hemodialysis study, using ^14C timolol added to human plasma or whole blood, showed that timolol was readily dialyzed from these fluids; however, a study of patients with renal failure showed that timolol did not dialyze readily.

DOSAGE AND ADMINISTRATION

TIMOPTIC Ophthalmic Solution is available in concentrations of 0.25 and 0.5%. The usual starting dose is one drop of TIMOPTIC 0.25% in the affected eye(s) twice a day. If the clinical response is not adequate, the dosage may be changed to one drop of 0.5% solution in the affected eye(s) twice a day.

Since in some patients the pressure-lowering response to TIMOPTIC may require a few weeks to stabilize, evaluation should include a determination of intraocular pressure after approximately 4 weeks of treatment with TIMOPTIC.

If the intraocular pressure is maintained at satisfactory levels, the dosage schedule may be changed to one drop once a day in the affected eye(s). Because of diurnal variations in intraocular pressure, satisfactory response to the once-a-day dose is best determined by measuring the intraocular pressure at different times during the day.

Dosages above one drop of TIMOPTIC 0.5% twice a day generally have not been shown to produce further reduction in intraocular pressure. If the patient's intraocular pressure is still not at a satisfactory level on this regimen, concomitant therapy with other agent(s) for lowering intraocular pressure can be instituted. The concomitant use of two topical beta-adrenergic blocking agents is not recommended [see PRECAUTIONS, Drug Interactions, Beta-adrenergic blocking agents].

HOW SUPPLIED

TIMOPTIC® (timolol maleate ophthalmic solution) is a clear, colorless to light yellow solution.

TIMOPTIC 0.25% timolol equivalent is supplied in a white low density polyethylene (LDPE) bottle with a controlled drop tip and a yellow polypropylene cap as follows:

NDC 24208-812-05: 5 mL in a 7.5 mL capacity bottle

TIMOPTIC 0.5% timolol equivalent is supplied in a white low density polyethylene (LDPE) bottle with a controlled drop tip and a yellow polypropylene cap as follows:

NDC 24208-813-05: 5 mL in a 7.5 mL capacity bottle
NDC 24208-813-10: 10 mL in a 10 mL capacity bottle

Storage

Store at 15°C to 25°C (59°F to 77°F). Protect from freezing. Protect from light. After opening, TIMOPTIC can be used until the expiration date on the bottle.

Distributed by:

Bausch & Lomb Americas Inc.
Bridgewater, NJ 08807 USA

TIMOPTIC is a trademark of Bausch & Lomb Incorporated or its affiliates.

© 2022 Bausch & Lomb Incorporated or its affiliates

Revised: 04/2022

9667803 (L-500346)
9667903 (L-500347)

Instructions for Use

TIMOPTIC® (tim-op´tik)

(timolol maleate ophthalmic solution) 0.25% and 0.5%

Read this Instructions for Use that comes with TIMOPTIC before you start using it and each time you get a refill. There may be new information. This information does not take the place of talking with your doctor about your medical condition or treatment.

Important information about TIMOPTIC:

• Use TIMOPTIC exactly as your doctor tells you to use it. Your doctor will tell you how much TIMOPTIC to use and when to use it.

• If you use other medicines in your eye, wait at least 10 minutes between using TIMOPTIC and your other eye medicines.

• Do not touch your eye or areas around your eye with the tip of the TIMOPTIC bottle. You may get bacteria on the tip of the bottle that can cause you to get an eye infection that can lead to serious eye damage or vision loss.

How should I use TIMOPTIC?

Step 1. Wash your hands.

Step 2. Turn your closed bottle of TIMOPTIC upside down (invert) and shake once.

Step 3. Remove the TIMOPTIC cap by turning the cap in the direction of the arrows shown (See Figure A). Put the cap in a clean and dry area. Do not let the tip of the bottle touch your fingers or other surfaces.

Figure A

Step 4. Hold the bottle between your thumb and index finger with 1 hand. Use the index finger of the other hand to pull down the lower eyelid to form a pocket for the eye drop (See Figure B). Tilt your head backwards.

Figure B

Step 5. Place the tip of the bottle close to your eye. Be careful not to touch your eye with the tip of the bottle. Gently squeeze the bottle and let 1 drop fall into the space between your lower eyelid and your eye (See Figure C). If a drop misses your eye, follow the instructions in steps 4 and 5 again.

Figure C

Step 6. If your doctor has told you to use TIMOPTIC in both eyes, repeat steps 4 and 5 for your other eye.

Step 7. Put the cap back on the bottle and close.

• The TIMOPTIC bottle tip is made to give 1 drop at a time. Do not try to make the hole in the tip of your bottle bigger.
• Do not wash the bottle tip.
• After you have used all of your TIMOPTIC doses, there will be some TIMOPTIC left in the bottle. Do not try to remove the extra TIMOPTIC from the bottle. Throw it away.

How should I store TIMOPTIC?

• Store TIMOPTIC at room temperature between 59°F to 77°F (15°C to 25°C) in an upright position.
• Do not freeze TIMOPTIC.
• Keep TIMOPTIC out of light.

Keep TIMOPTIC and all medicines out of the reach of children.

If you would like more information, talk with your doctor. You can ask your pharmacist or doctor for more information about TIMOPTIC that is written for health professionals.

This Instructions for Use has been approved by the U.S. Food and Drug Administration.

Distributed by:
Bausch & Lomb Americas Inc.
Bridgewater, NJ 08807 USA

TIMOPTIC is a trademark of Bausch & Lomb Incorporated or its affiliates.

© 2022 Bausch & Lomb Incorporated or its affiliates

Revised: 04/2022

9667803 (L-500346)
9667903 (L-500347)

PACKAGE/LABEL PRINCIPAL DISPLAY PANEL - 0.25% Carton

NDC 24208-812-05

TIMOPTIC®
(timolol maleate
ophthalmic solution)

0.25%

Timolol Equivalent
(timolol maleate 3.4 mg/mL
equivalent to 2.5 mg/mL timolol)

Sterile

FOR TOPICAL
OPHTHALMIC USE

Rx only

5 mL

BAUSCH + LOMB

9451705
AB33007

PACKAGE/LABEL PRINCIPAL DISPLAY PANEL - 0.5% Carton

NDC 24208-813-05

TIMOPTIC®
(timolol maleate
ophthalmic solution)

0.5%

Timolol Equivalent
(timolol maleate 6.8 mg/mL
equivalent to 5 mg/mL timolol)

Sterile

FOR TOPICAL
OPHTHALMIC USE

Rx only

5 mL

BAUSCH + LOMB

9451905
AB32407